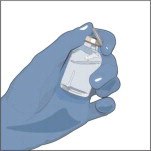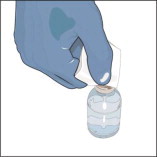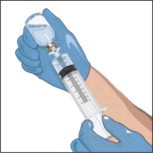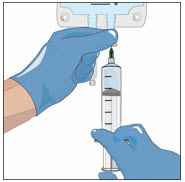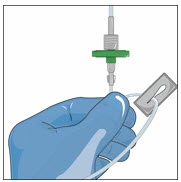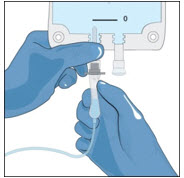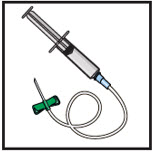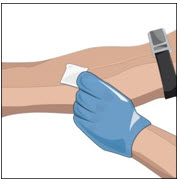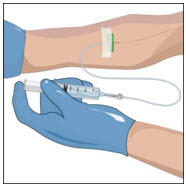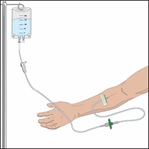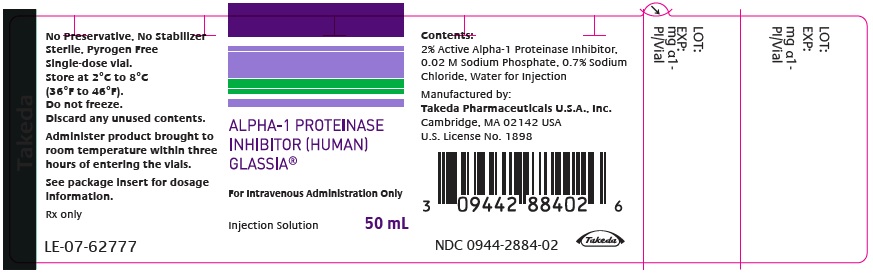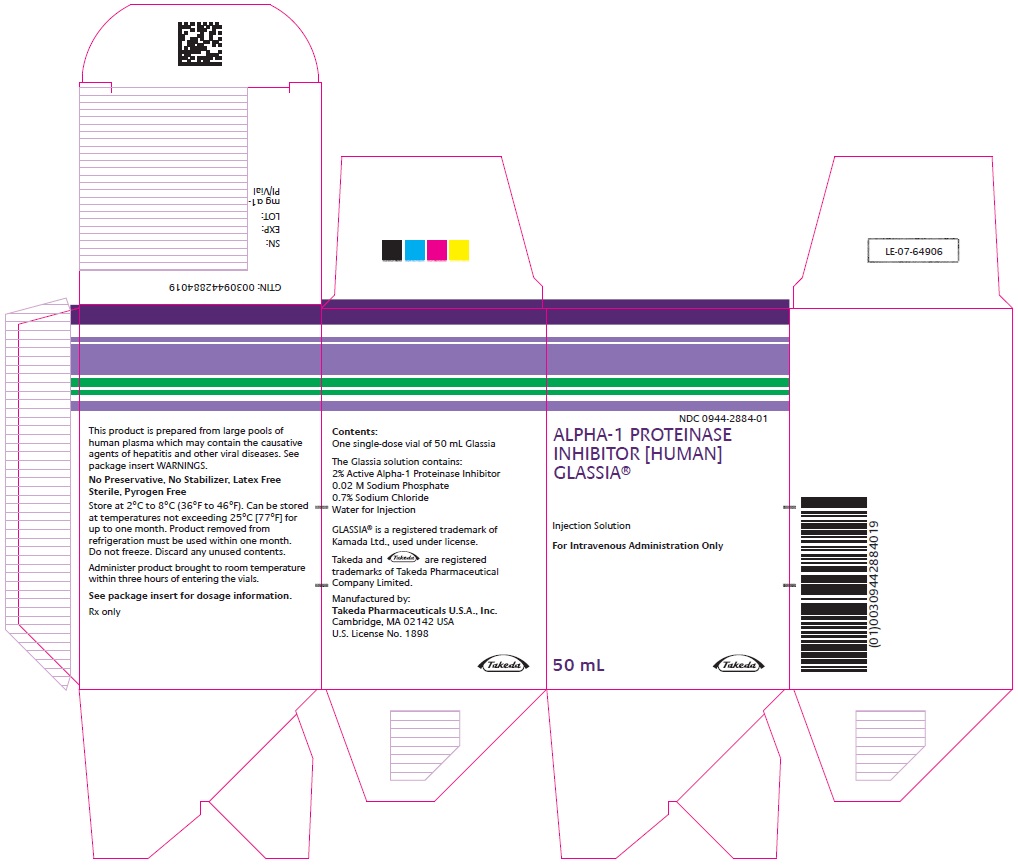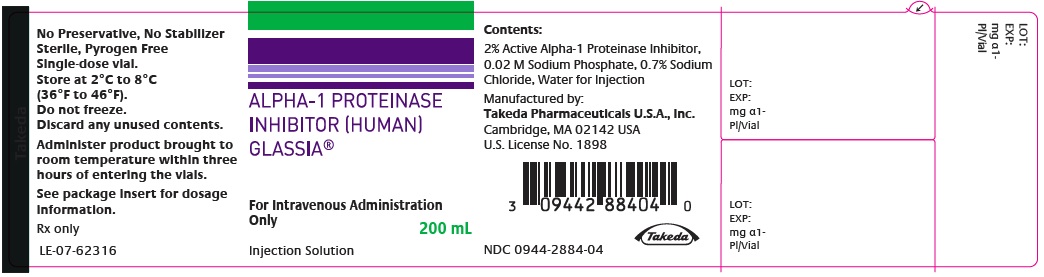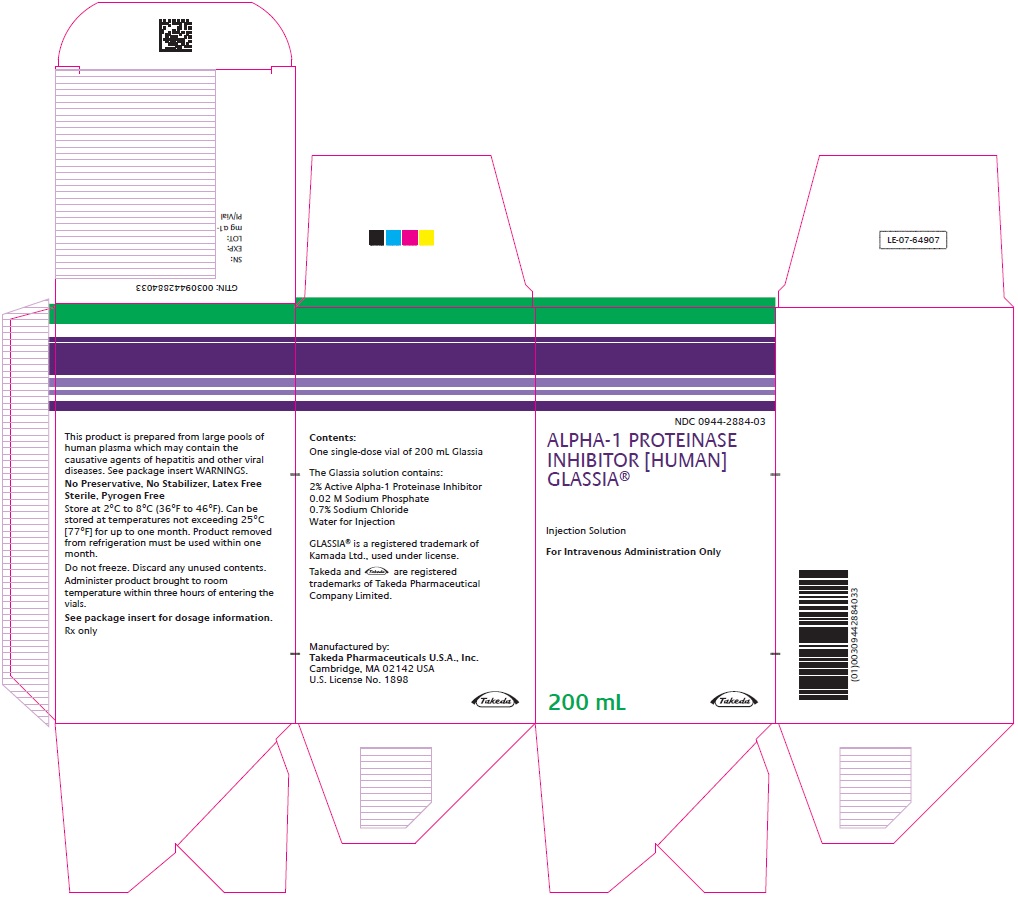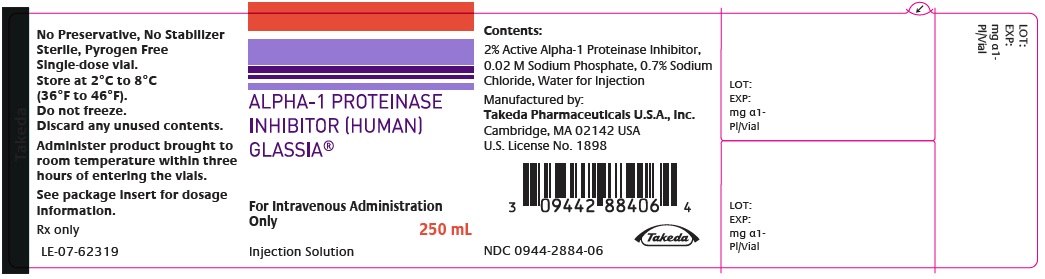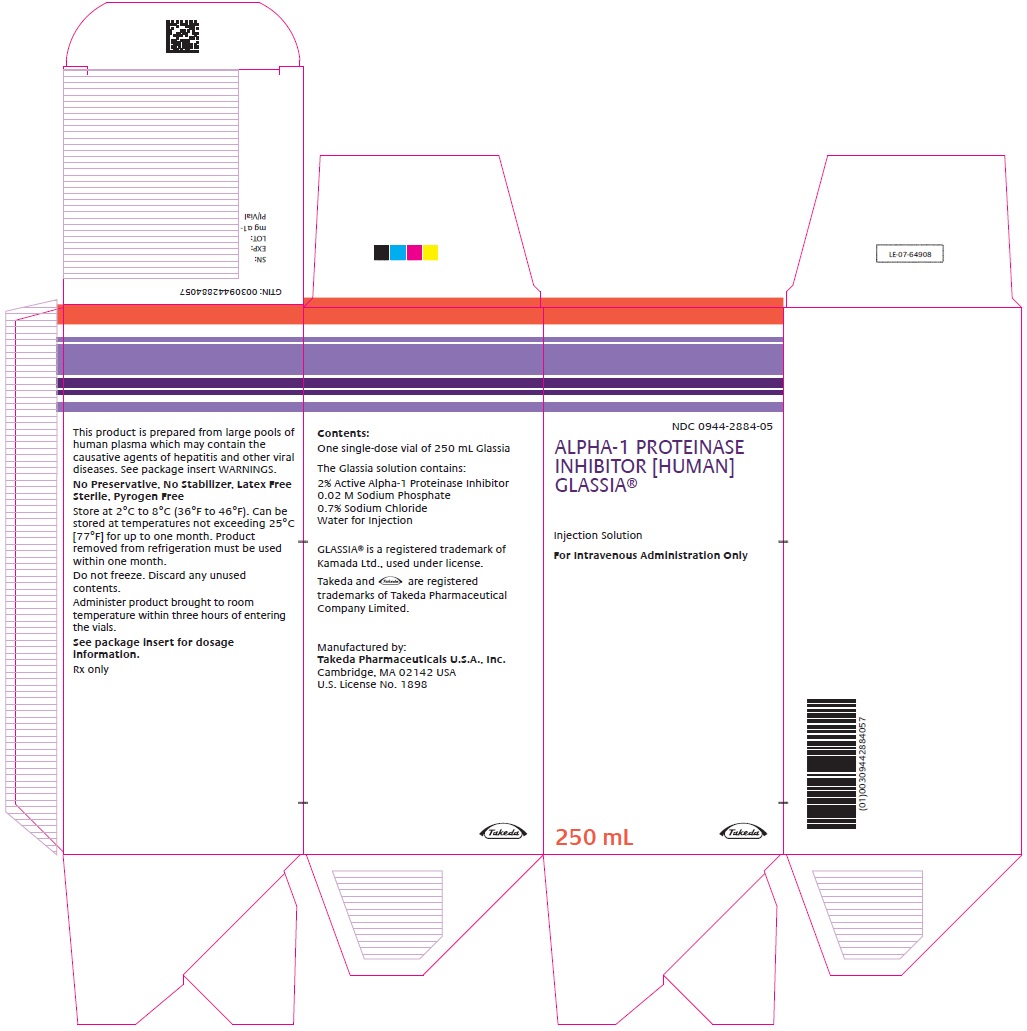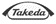 DRUG LABEL: GLASSIA
NDC: 0944-2884 | Form: INJECTION, SOLUTION
Manufacturer: Takeda Pharmaceuticals America, Inc.
Category: other | Type: PLASMA DERIVATIVE
Date: 20251202

ACTIVE INGREDIENTS: .ALPHA.1-PROTEINASE INHIBITOR HUMAN 1 g/50 mL
INACTIVE INGREDIENTS: SODIUM PHOSPHATE, MONOBASIC, DIHYDRATE; SODIUM CHLORIDE; WATER

HIGHLIGHTS OF PRESCRIBING INFORMATION

These highlights do not include all the information needed to use GLASSIA safely and effectively. See full prescribing information for GLASSIA.
GLASSIA® (Alpha1-Proteinase Inhibitor (Human))
Injection, For Intravenous Use
Initial U.S. Approval: 2010

RECENT MAJOR CHANGES

Dosage and Administration, Administration (2.3) | 2/2025

1 INDICATIONS AND USAGE

GLASSIA is an Alpha1-Proteinase Inhibitor (Human) (Alpha1-PI) indicated for chronic augmentation and maintenance therapy in adults with clinically evident emphysema due to severe hereditary deficiency of Alpha1-PI (alpha1-antitrypsin deficiency). (1)

Limitations of Use:

- The effect of augmentation therapy with any Alpha1-PI, including GLASSIA, on pulmonary exacerbations and on the progression of emphysema in alpha1-antitrypsin deficiency has not been conclusively demonstrated in randomized, controlled clinical trials. (1)
- Clinical data demonstrating the long-term effects of chronic augmentation and maintenance therapy of individuals with GLASSIA are not available. (1)
- GLASSIA is not indicated as therapy for lung disease in patients in whom severe Alpha1-PI deficiency has not been established. (1)

2 DOSAGE AND ADMINISTRATION

For intravenous use only. (2)

- Dose = 60 mg/kg body weight intravenously once weekly. (2.1)
- Administer at a rate not to exceed 0.2 mL/kg body weight per minute, depending on patient response and comfort. (2.3)
- Dose ranging studies using efficacy endpoints have not been performed. (2.1)
- Always use a 5 micron in-line filter (minimum filter diameter of 32 mm to ensure optimal performance, not supplied) during infusion. (2.3)
- If adverse events occur, reduce the rate or interrupt the infusion until the symptoms subside. Resume the infusion at a rate tolerated by the patient. (2.3)

3 DOSAGE FORMS AND STRENGTHS

For injection: Approximately 1 gram, 4 gram and 5 gram of functional Alpha1-PI in ready to use solution in a single-dose vial. GLASSIA is available in the following vial volumes: 50 mL, 200 mL and 250 mL, respectively. (3)

4 CONTRAINDICATIONS

- IgA deficient patients with antibodies against IgA. (4)
- History of anaphylaxis or other severe systemic reaction, to Alpha1-PI products. (4)

5 WARNINGS AND PRECAUTIONS

- Severe hypersensitivity and anaphylactic reactions may occur in IgA deficient patients with antibodies against IgA and in patients with a history of hypersensitivity to other Alpha1-PI products. (5.1)
- May carry a risk of transmitting infectious agents such as viruses, the variant Creutzfeldt-Jakob disease (vCJD) and theoretically, the Creutzfeldt-Jakob disease (CJD) agent. (5.2)

6 ADVERSE REACTIONS

The most common adverse reactions in clinical trials were headache and upper respiratory infection. (6)

To report SUSPECTED ADVERSE REACTIONS, contact Takeda Pharmaceuticals U.S.A., Inc. at 1-877-TAKEDA-7 (1-877-825-3327) or FDA at 1-800-FDA-1088 or www.fda.gov/medwatch.

FULL PRESCRIBING INFORMATION

1 INDICATIONS AND USAGE

GLASSIA is an Alpha1-Proteinase Inhibitor (Human), indicated for chronic augmentation and maintenance therapy in individuals with clinically evident emphysema due to severe hereditary deficiency of Alpha1-PI, also known as alpha1-antitrypsin (AAT) deficiency.

Limitations of Use:

- The effect of augmentation therapy with GLASSIA or any Alpha1-PI product on pulmonary exacerbations and on the progression of emphysema in Alpha1-PI deficiency has not been conclusively demonstrated in randomized, controlled clinical trials.
- Clinical data demonstrating the long-term effects of chronic augmentation and maintenance therapy of individuals with GLASSIA are not available.
- GLASSIA is not indicated as therapy for lung disease in patients in whom severe Alpha1-PI deficiency has not been established.

2 DOSAGE AND ADMINISTRATION

For intravenous use only.

2.1 Dosage

- Administer 60 mg/kg body weight of GLASSIA once weekly by intravenous infusion.
- Dose ranging studies using efficacy endpoints have not been performed.
- The carton and label on each vial of GLASSIA show the actual amount of functionally active Alpha1-PI in milligrams.

2.2 Preparation

1. Use aseptic technique.
2. Allow the product to reach room temperature prior to infusing and administer within three hours of entering the vials.
3. Inspect the vial of GLASSIA. The solution should be clear and colorless to yellow-green and may contain a few protein particles. Discard if the product is cloudy.
4. The product is suitable for infusion directly from the vial or pooled into a sterile container for intravenous infusion.
5. Use a vented spike (not supplied) to withdraw the solution from the vial.
6. Then use a needle (not supplied) to transfer the solution into the intravenous infusion container.
7. If using multiple vials to achieve the desired dose, pool GLASSIA into the infusion container by repeating Steps 5 and 6 with a new vented spike and transfer needle for each vial.

2.3 Administration

For intravenous infusion only.

GLASSIA should be administered by a healthcare professional or self-administered by the patient/caregiver after appropriate training. For self-administration, provide the patient/caregiver with detailed instructions and adequate training for infusion in the home or other appropriate setting [see Patient Counseling Information (17)].

1. Use aseptic technique.
2. Inspect parenteral products visually for particulate matter and discoloration prior to administration whenever solution and container permit.
3. Administer GLASSIA alone. Do not mix with other agents or diluting solutions.
4. When infusing directly from the vials, use a vented spike (not supplied). Peel clear plastic hanger from vial label. Hang on IV pole and administer product. If the contents of vials have been pooled to a sterile intravenous container, use an appropriate intravenous administration set.
5. Always use a 5 micron in-line filter (minimum filter diameter of 32 mm to ensure optimal performance, not supplied) during infusion.
6. Administer GLASSIA within three hours of entering the vials to avoid the potential ill effect of any inadvertent microbial contamination.
7. Administer GLASSIA at room temperature through an appropriate intravenous administration set at a rate not to exceed 0.2 mL/kg body weight per minute, and as determined by the response and comfort of the patient. The recommended dosage of 60 mg/kg at a rate of 0.2 mL/kg/min will take approximately 15 minutes to infuse.
8. Monitor the infusion rate closely during administration and observe the patient for signs of infusion related reactions. If infusion related adverse reactions occur, reduce the rate or interrupt the infusion as appropriate until the symptoms subside. Resume the infusion at a rate tolerated by the patient, except in the case of severe reaction [see Warnings and Precautions (5.1)].
9. Following administration, discard all open vials, unused solution and administration equipment.

3 DOSAGE FORMS AND STRENGTHS

GLASSIA is available as a single-dose vial containing approximately 1 gram, 4 gram, and 5 gram of functional Alpha1-PI in 50 mL, 200 mL and 250 mL of ready to use solution.

4 CONTRAINDICATIONS

GLASSIA is contraindicated in:

- immunoglobulin A (IgA) deficient patients with antibodies against IgA.
- individuals with a history of anaphylaxis or other severe systemic reaction to Alpha1-PI products.

5 WARNINGS AND PRECAUTIONS

5.1 Hypersensitivity Reactions

GLASSIA may contain trace amounts of IgA. Patients with known antibodies to IgA, which can be present in patients with selective or severe IgA deficiency, have a greater risk of developing severe hypersensitivity and anaphylactic reactions. Monitor vital signs continuously and observe the patient carefully throughout the infusion. Discontinue the infusion if hypersensitivity symptoms occur and administer appropriate emergency treatment. Have epinephrine and/or other appropriate supportive therapy available for the treatment of any acute anaphylactic or anaphylactoid reaction.

5.2 Transmissible Infectious Agents

Because this product is made from human plasma, it may carry a risk of transmitting infectious agents, such as viruses, the variant Creutzfeldt-Jakob disease (vCJD) and theoretically, the Creutzfeldt-Jakob disease (CJD) agent. This also applies to unknown or emerging viruses and other pathogens. The risk of transmitting an infectious agent has been minimized by screening plasma donors for prior exposure to certain viruses, by testing for the presence of certain current virus infections and by inactivating and removing certain viruses during the manufacturing process. Despite these measures, such products may still potentially transmit human pathogenic agents.

All infections thought by a physician possibly to have been transmitted by this product should be reported by the physician or other healthcare provider to Takeda Pharmaceuticals U.S.A., Inc. at 1-877-TAKEDA-7 (1-877-825-3327) or FDA at 1-800-FDA-1088 or www.fda.gov/medwatch.

No seroconversions for hepatitis B or C (HBV or HCV) or human immunodeficiency virus (HIV) or any other known infectious agent were reported with the use of GLASSIA during the clinical trials.

6 ADVERSE REACTIONS

The serious adverse reaction observed during clinical trials with GLASSIA was exacerbation of chronic obstructive pulmonary disease (COPD).

The most common adverse reactions during clinical trials were headache and upper respiratory infection.

6.1 Clinical Trials Experience

Because clinical trials are conducted under widely varying conditions, adverse reaction rates observed in the clinical trials of a drug cannot be directly compared to rates in the clinical trials of another drug and may not reflect the rates observed in clinical practice.

The safety profile of GLASSIA was evaluated in a randomized, double-blind, active-control trial and an open-label, non-parallel, dose-escalation trial, in 65 subjects with pre-augmentation therapy serum Alpha1-PI levels less than 11 microM. In the randomized, double-blind, active-control trial, 50 subjects received weekly infusions of GLASSIA or the comparator Alpha1-PI product, Prolastin, at a dosage of 60 mg/kg for a total of 12 doses after which all subjects remaining in the trial were treated for another 12 weeks with GLASSIA only. Overall, 17 subjects received 12 doses and 32 subjects received 22 - 24 doses of GLASSIA during the trial. (One subject randomized to the comparator Alpha1-PI product did not receive any treatment with GLASSIA during the last 12 weeks of the trial.). In the open label, non-parallel, dose-escalation trial, 18 subjects received a single infusion of GLASSIA at dosages of 30, 60 or 120 mg/kg. The population treated in the two trials was 40-74 years old, 54% male, 100% Caucasian.

Tables 1 and 2 compare the adverse reactions reported during the initial 12 weeks (double-blind portion) of the randomized, active comparator trial in all subjects treated with GLASSIA with reactions in the concurrent Prolastin control group. Table 3 compares the frequency of adverse reactions as a percentage of all infusions for GLASSIA and Prolastin-treated subjects over the entire trial period.

Table 1: Number of Subjects/Infusions/Adverse Reactions [An adverse reaction is any adverse event which met any of the following criteria: (a) an adverse event that began within 72 hours following the end of product infusion, or (b) an adverse event considered by either the investigator or sponsor to be at least possibly related to product administration, or (c) an adverse event for which causality assessment was missing or indeterminate.] Occurring during the First 12 Weeks of Treatment
Assessed Parameters | GLASSIA | Prolastin
No. of subjects treated | 33 | 17
No. of infusions | 393 | 190
No. of subjects with serious adverse reactions (%) | 1 (3%) | 1 (6%)
No. of subjects experiencing an adverse reaction (%) | 22 (67%) | 15 (88%)
No. of adverse reactions | 47 | 39

Table 2: Adverse Reactions [An adverse reaction is any adverse event which met any of the following criteria: (a) an adverse event that began within 72 hours following the end of product infusion, or (b) an adverse event considered by either the investigator or sponsor to be at least possibly related to product administration, or (c) an adverse event for which causality assessment was missing or indeterminate.] Occurring in > 5% of Subjects during the First 12 Weeks of Treatment
Adverse Reactions (AR) | GLASSIA (N=33) No. of subjects with adverse reactions (AR) (percentage of all subjects) | Prolastin (N=17) No. of subjects with adverse reactions (AR) (percentage of all subjects)
Cough | 3 (9%) | 4 (24%)
Headache | 3 (9%) | 3 (18%)
Sinusitis | 3 (9%) | 1 (6%)
Upper respiratory tract infection | 3 (9%) | 0 (0%)
Chest discomfort | 2 (6%) | 0 (0%)
Dizziness | 2 (6%) | 0 (0%)
Hepatic enzyme increased | 2 (6%) | 0 (0%)

Table 3: Adverse Reactions [An adverse reaction is any adverse event which met any of the following criteria: (a) an adverse event that began within 72 hours following the end of product infusion, or (b) an adverse event considered by either the investigator or sponsor to be at least possibly related to product administration, or (c) an adverse event for which causality assessment was missing or indeterminate.] Frequency as a % of all Infusions (≥ 0.5%)
Adverse Reactions (AR) | GLASSIA [Throughout entire 24-week double-blind plus open-label trial period.] (Ni=960) No. of adverse reactions (AR) (percentage of all infusions) | Prolastin [Throughout initial 12-week double-blind period.] (Ni=190) No. of adverse reactions (AR) (percentage of all infusions)
Upper respiratory tract infection | 8 (0.8%) | 0 (0.0%)
Headache | 6 (0.6%) | 3 (1.6%)
Nasopharyngitis | 5 (0.5%) | 0 (0%)
Ni=number of infusions.

Chronic Obstructive Pulmonary Disease (COPD) Exacerbations

During the 12-week double blind portion of the randomized, active comparator trial, 4 subjects (12%) had a total of 7 exacerbations of chronic obstructive pulmonary disease (COPD) during GLASSIA treatment and 5 subjects (29%) had a total of 6 exacerbations of COPD during Prolastin treatment. Seventeen additional exacerbations in 14 subjects (28%) occurred during the 12-week open-label treatment period with GLASSIA. The overall rate of pulmonary exacerbations during treatment with either product was 1.3 exacerbations per subject per year. Testing for viral markers for HBV, HCV, HIV-1 and HIV-2 showed no seroconversions during either trial.

Immunogenicity

As with all therapeutic proteins, there is a potential for immunogenicity. The detection of antibody formation is highly dependent on the sensitivity and specificity of the assay. Additionally, the observed incidence of antibody (including neutralizing antibody) positivity in an assay may be influenced by several factors including assay methodology, sample handling, timing of sample collection, concomitant medications, and underlying disease. For these reasons, comparison of the incidence of antibodies to GLASSIA with the incidence of antibodies to other products may be misleading.

In the double blind, randomized, active comparator trial of GLASSIA, low level anti-GLASSIA antibodies were detected in one subject at one time point (Week 12) and returned to negative at the end of the study (Week 24) despite continuous exposure to GLASSIA. No immune system adverse reactions were reported.

Immunogenicity was further evaluated in the multicenter study (post-licensure) in subjects with Alpha1-PI deficiency. Of the 34 subjects studied, 2 (6%) developed neutralizing anti-Alpha1-PI antibodies. There was no association between patients with Alpha1-PI antibodies and immune-mediated treatment emergent adverse reactions or associated decrease in plasma Alpha1-PI levels.

6.2 Postmarketing Experience

The following adverse reactions have been identified during post-approval use of GLASSIA. Because these reactions are reported voluntarily from a population of uncertain size, it is not always possible to reliably estimate their frequency or establish a causal relationship to drug exposure.

Respiratory, Thoracic, and Mediastinal Disorders: Dyspnea

Gastrointestinal Disorders: Nausea

General Disorders and Administration Site Conditions: Fatigue

8 USE IN SPECIFIC POPULATIONS

8.1 Pregnancy

Risk Summary

There are no data with GLASSIA use in pregnant women to inform a drug-associated risk. Animal reproduction studies have not been conducted with GLASSIA. It is also not known whether GLASSIA can cause fetal harm when administered to pregnant women or can affect reproductive capacity. GLASSIA should be given to a pregnant woman only if clearly needed.

8.2 Lactation

Risk Summary

There is no information regarding the presence of GLASSIA in human milk, the effect on the breastfed infant, or the effects on milk production. The developmental and health benefits of breastfeeding should be considered along with the mother's clinical need for GLASSIA and any potential adverse effects on the breastfed infant from GLASSIA.

8.4 Pediatric Use

Safety and effectiveness in pediatric patients have not been established.

8.5 Geriatric Use

Clinical trials of GLASSIA included 11 subjects of 65 years of age or older. This number of subjects was not sufficient to determine whether they respond differently from younger subjects. As for all patients, dosing for geriatric patients should be appropriate to their overall situation. Safety and effectiveness in patients over 65 years of age have not been established.

11 DESCRIPTION

GLASSIA is a sterile, ready to use, liquid preparation of purified human Alpha1-proteinase inhibitor (Alpha1-PI), also known as alpha1-antitrypsin (AAT). The solution contains 2% active Alpha1-PI in a phosphate-buffered saline solution. The specific activity of GLASSIA is ≥ 0.7 mg functional Alpha1-PI per mg of total protein. Not less than 90% of the Alpha1-PI in GLASSIA is of the monomeric form as measured by size-exclusion chromatography.

GLASSIA is prepared from human plasma obtained from US-licensed plasma collection centers by a modified version of the cold ethanol fractionation process and the Alpha1-PI is then purified using chromatographic methods.

Individual plasma units used for production of GLASSIA are tested using FDA- licensed serological assays for hepatitis B surface antigen (HBsAg) and for antibodies to hepatitis C virus (HCV) and human immunodeficiency virus types 1 and 2 (HIV-1/2), as well as by FDA-licensed Nucleic Acid Testing (NAT) for HCV and HIV-1. Each plasma unit must be non-reactive (negative) in all tests. Plasma is also tested by in-process NAT procedures for parvovirus B19 and the limit for B19 DNA in the manufacturing pool is set not to exceed 10^4 IU per mL.

To reduce the risk of viral transmission, the manufacturing process for GLASSIA includes two steps specifically designed to remove or inactivate viruses. The first of these is nanofiltration (NF) through a 15 nm filter which can remove both enveloped and non–enveloped viral agents and the second is solvent/detergent (S/D) treatment with a mixture of tri-(n-butyl) phosphate (TNBP) and Polysorbate 80 (Tween 80) which inactivates enveloped viral agents such as HIV, HBV and HCV.

The effectiveness of the S/D treatment and nanofiltration procedures for reducing virus content has been assessed using a series of viruses with a range of physico-chemical characteristics. The results of the viral challenge studies are summarized in Table 4.

Table 4: Log10 Virus Reduction during Manufacture of GLASSIA
Process Step | Enveloped Viruses HIV-1 | Enveloped Viruses PRV | Enveloped Viruses BVDV | Enveloped Viruses WNV | Non-enveloped Viruses HAV | Non-enveloped Viruses PPV
Nanofiltration | > 5.59 | > 5.57 | > 5.74 | ND | > 4.99 | 4.04
S/D treatment | > 6.41 | > 6.14 | > 5.61 | > 6.32 | N/A | N/A
Global Reduction Factor | > 12.00 | > 11.71 | > 11.35 | > 6.32 | > 4.99 | 4.04
N/A - Not Applicable. The S/D treatment is not relevant for non-enveloped viruses.
ND - Not Done

HIV-1 | Human immunodeficiency virus Type 1 | WNV | West Nile virus
PRV | Pseudorabies virus | HAV | Hepatitis A virus
BVDV | Bovine viral diarrhea virus | PPV | Porcine parvovirus

12 CLINICAL PHARMACOLOGY

12.1 Mechanism of Action

GLASSIA administration is intended to inhibit serine proteases such as neutrophil elastase (NE), which is capable of degrading protein components of the alveolar walls and which is chronically present in the lung.

Alpha1-PI deficiency is a chronic, autosomal, co-dominant hereditary disorder characterized by reduced levels of Alpha1-PI in the blood and lungs^(1, 2). Smoking is an important risk factor for the development of emphysema in patients with Alpha1-PI deficiency^3. Because emphysema affects many, but not all individuals with the more severe genetic variants of Alpha1-PI deficiency (AAT deficiency), augmentation therapy with Alpha1-Proteinase Inhibitor (Human) is indicated only in patients with severe Alpha1-PI deficiency who have clinically evident emphysema.

A large number of phenotypic variants of Alpha1-PI deficiency exist, not all of which are associated with the clinical disease. Approximately 95% of identified Alpha1-PI deficient individuals have the PiZZ variant, typically characterized by Alpha1-PI serum levels < 35% of normal. Individuals with the Pi(null)(null) variant have no Alpha1-PI protein in their serum^(2, 3). Individuals with the lack of, or low, endogenous serum levels of Alpha1-PI, i.e., below 11 μM, manifest a significantly increased risk for development of emphysema above the general population background risk^(4, 5). In addition, PiSZ individuals, whose serum Alpha1-PI levels range from approximately 9 to 23 μM are considered to have moderately increased risk for developing emphysema, regardless of whether their serum Alpha1-PI levels are above or below 11 μM^6.

Augmenting the levels of functional protease inhibitor by intravenous infusion is an approach to therapy for patients with Alpha1-PI deficiency. However, the efficacy of augmentation therapy in affecting the progression of emphysema has not been demonstrated in randomized, controlled clinical trials. The intended theoretical goal is to provide protection to the lower respiratory tract by correcting the imbalance between neutrophil elastase and protease inhibitors. Whether augmentation therapy with GLASSIA or any Alpha1-PI product actually protects the lower respiratory tract from progressive emphysematous changes has not been conclusively demonstrated in adequately powered, randomized controlled clinical trials. Although the maintenance of blood serum levels of Alpha1-PI (antigenically measured) above 11 μM has been historically postulated to provide therapeutically relevant anti-neutrophil elastase protection, this has not been proven. Individuals with severe Alpha1-PI deficiency have been shown to have increased neutrophil and neutrophil elastase concentrations in lung epithelial lining fluid compared to normal PiMM individuals, and some PiSZ individuals with Alpha1-PI above 11 μM have emphysema attributed to Alpha1-PI deficiency. These observations underscore the uncertainty regarding the appropriate therapeutic target serum level of Alpha1-PI during augmentation therapy.

12.2 Pharmacodynamics

Administration of GLASSIA to patients with Alpha1-PI deficiency augments the level of the deficient protein. Normal individuals have levels of Alpha1-PI greater than 22 μM. The clinical benefit of the increased blood levels of Alpha1-PI at the recommended dose has not been established.

The clinical efficacy of GLASSIA in influencing the course of pulmonary emphysema or the frequency, duration, or severity of pulmonary exacerbations has not been demonstrated in randomized, controlled clinical trials.

GLASSIA increases antigenic and functional (anti-neutrophil elastase capacity, ANEC) levels of Alpha1-PI in both the serum and the lung epithelial lining fluid (ELF) [see Clinical Studies (14)].

12.3 Pharmacokinetics

A prospective, open-label, uncontrolled multicenter pharmacokinetic trial was conducted in 7 females and 11 males with congenital Alpha1-PI deficiency, ranging in age from 40 to 69 years. Subjects received a single dose of GLASSIA either 30 mg/kg, 60 mg/kg or 120 mg/kg. Blood samples for pharmacokinetic study were taken prior to and within 5 minutes of completion of the infusion, and then at 1 hour, 6 hours, 12 hours, 24 hours, 3 days and 7 days.

The mean results for pharmacokinetic parameters in the 60 mg/kg dosage group are shown in Table 5. The pharmacokinetics of GLASSIA were linear over the dose range of 30-120 mg/kg.

Table 5: Pharmacokinetic Parameters for Functional Alpha1-PI (Dosage 60 mg/kg; n=6)
Pharmacokinetic Parameter | 60 mg/kg Dose Group
Terminal Half-Life (h) [Any assessment of the clinical relevance of half-life in this trial should be viewed with caution, due to the short duration of blood sampling.] | 111 ± 33
Area under the curve(0-168 h) (mg∙h/mL) | 89 ± 10
Clearance (mL/h/kg) | 0.68 ± 0.1
Volume of Distribution (L) | 3.2 ± 0.3

14 CLINICAL STUDIES

A randomized, double-blind trial with a partial cross-over was conducted to compare GLASSIA to a commercially available preparation of Alpha1-PI (Prolastin) in 50 Alpha1-PI-deficient subjects. The trial objectives were to demonstrate that the pharmacokinetics of antigenic and/or functional Alpha1-PI in GLASSIA were not inferior to those of the control product, to determine whether GLASSIA maintained antigenic and/or functional plasma levels of at least 11 microM (57 mg/dL) and to compare Alpha1-PI trough levels (antigenic and functional) over 6 infusions.

For inclusion in the trial, subjects were required to have lung disease related to Alpha1-PI deficiency and 'at-risk' alleles associated with Alpha1-PI plasma levels < 11 microM. Subjects already receiving Alpha1-PI therapy were required to undergo a 5-week wash-out period of exogenous Alpha1-PI prior to dosing.

Fifty subjects received either GLASSIA (33 subjects) or the comparator product (17 subjects) at a dose of 60 mg/kg intravenously per week for 12 consecutive weeks. From Week 13 to Week 24 all subjects received open-label weekly infusions of GLASSIA at a dose of 60 mg/kg.

Trough levels of functional and antigenic Alpha1-PI were measured prior to treatment, at baseline and throughout the trial until Week 24. The median trough Alpha1-PI values for Weeks 7-12 for subjects receiving GLASSIA were 14.5 microM (range: 11.6 to 18.5 microM) for antigenic and 11.8 microM (range: 8.2 to 16.9 microM) for functional Alpha1-PI. Eleven of 33 subjects (33.3%) receiving GLASSIA had mean steady-state functional Alpha1-PI levels below 11 microM. GLASSIA was shown to be non-inferior to the comparator product.

Serum Alpha1-PI trough levels rose substantially in all subjects by Week 2 and were comparatively stable during Weeks 7 to 12. All subjects receiving GLASSIA had mean serum trough antigenic Alpha1-PI levels greater than 11 microM during Weeks 7-12.

A subset of subjects in both treatment groups (n = 7 for subjects receiving GLASSIA) underwent broncho-alveolar lavage (BAL) and were shown to have increased levels of antigenic Alpha1-PI and Alpha1-PI - neutrophil elastase complexes in the epithelial lining fluid at Week 10-12 over levels found at baseline, demonstrating the ability of the product to reach the lung.

The clinical efficacy of GLASSIA in influencing the course of pulmonary emphysema or the frequency, duration, or severity of pulmonary exacerbations has not been demonstrated in randomized, controlled clinical trials.

A prospective, randomized, double-blind, active-controlled, crossover trial was conducted in thirty healthy adult subjects (23 [77%] male and 7 [23%] female; median age of 24 years [range: 19 to 61 years]), each receiving 2 infusions of GLASSIA at a dosage of 60 mg/kg. The objective of the trial was to assess the safety and tolerability of GLASSIA at an intravenous infusion rate of 0.2 mL/kg/min. On Day 1, 15 subjects received GLASSIA at 0.04 mL/kg/min with a simultaneous administration of placebo (2.5% human albumin in normal saline, for the purpose of masking infusion) at 0.2 mL/kg/min (Cohort 1), and 15 subjects received GLASSIA at 0.2 mL/kg/min with a simultaneous administration of placebo at 0.04 mL/kg/min (Cohort 2). Two weeks later (Day 15), the 15 subjects in Cohort 1 received the second infusion of GLASSIA at 0.2 mL/kg/min with a simultaneous administration of placebo at 0.04 mL/kg/min, and the 15 subjects in Cohort 2 received GLASSIA at 0.04 mL/kg/min with a simultaneous administration of placebo at 0.2 mL/kg/min. Neither efficacy nor exposure (antigenic or functional AAT) was measured in this trial.

The safety, immunogenicity, and effects on the Alpha1-PI levels in epithelial lining fluid (ELF) following GLASSIA therapy were evaluated in a multicenter study (post-licensure) of 34 subjects with emphysema due to congenital A1PI deficiency. Subjects received GLASSIA at a dosage of 60 mg/kg for 25 weeks. Sixteen subjects underwent bronchoalveolar lavage (BAL) at baseline and at Weeks 12-14. GLASSIA augmentation therapy resulted in a statistically significant increase in antigenic Alpha1-PI levels in ELF (median change=0.5 μM; geometric mean ratio=5.4, p<0.001; Table 6). Functional Alpha1-PI levels in ELF also showed a statistically significant increase in response to GLASSIA (median change=0.3 μM, geometric mean ratio=2.3, p<0.001; Table 6).

Table 6: Summary and Analysis of Change from Baseline in Antigenic and Functional Alpha1-PI Levels in the Epithelial Lining Fluid
Alpha1-PI Levels (n=16) | Geometric Mean [From a mixed-effects model with visit as fixed effect and subject as random effect; a 1-sided paired t-test for H0: Diff (On-Treatment BAL – Baseline BAL) ≤ 0 and H1: Diff (On-Treatment BAL – Baseline BAL) > 0.] Baseline BAL (µM) | Geometric Mean On-Treatment BAL (µM) (Weeks 12-14) | Geometric Mean Ratio (p-value)
Antigenic Alpha1-PI Levels | 0.1 | 0.6 | 5.4 (<0.001)
Functional Alpha1-PI Levels | 0.2 | 0.5 | 2.3 (<0.001)

15 REFERENCES

1. WHO. "α1-Antitrypsin deficiency." Memorandum from a WHO meeting. 1997;75: 397-415.
2. Stoller JK, et al. Augmentation therapy with α 1-antitrypsin: patterns of use and adverse events. Chest 2003; 123:1425-34.
3. Cox DW. α1-Antitrypsin Deficiency. In: Scriver C, Sly W, eds. The Metabolic and Molecular Bases of Inherited Disease. New York: McGraw Hill; 2002:5559-78.
4. Crystal RG, et al. The alpha1-antitrypsin gene and its mutations. Clinical consequences and strategies for therapy. Chest 1989;95:196-208.
5. Crystal RG. α1-Antitrypsin deficiency: pathogenesis and treatment. Hosp Pract (Off Ed) 1991;26:81-4, 8-9, 93-4.
6. Turino GM, et al. Clinical features of individuals with PI*SZ phenotype of α1-antitrypsin deficiency. Am J Respir Crit Care Med 1996;154:1718-25.

16 HOW SUPPLIED/STORAGE AND HANDLING

GLASSIA is supplied in a single-dose vial containing the labeled amount of functional active Alpha1-PI.

The following presentations of GLASSIA are available.

Carton NDC | Vial NDC | Grams Protein | Volume
0944-2884-01 | 0944-2884-02 | 1 g | 50 mL
0944-2884-03 | 0944-2884-04 | 4 g | 200 mL
0944-2884-05 | 0944-2884-06 | 5 g | 250 mL

- Store GLASSIA at 2°C to 8°C (36°F to 46°F). Do not freeze.
- Product may be stored at room temperatures not exceeding 25°C (77°F) for up to one month.
- Once removed from refrigeration use within one month.
- Keep vial in carton until required for use.
- Do not use after the expiration date printed on the label.
- GLASSIA contains no preservatives and no latex.

17 PATIENT COUNSELING INFORMATION

Advise the patient to read the FDA-approved patient labeling (Patient Information and Detailed Instructions for Administration).

- Inform patients of the early signs of hypersensitivity reactions, including hives, generalized urticaria, chest tightness, dyspnea, wheezing, faintness, hypotension, and anaphylaxis. Advise patients to discontinue use of the product and contact their physician and/or seek immediate emergency care, depending on the severity of the reaction, if these symptoms occur.
- Inform patients that GLASSIA is made from human plasma and may contain infectious agents that can cause disease (e.g., viruses and, theoretically, the CJD agent). Explain that the risk of GLASSIA transmitting an infectious agent has been reduced by screening the plasma donors, by testing the donated plasma for certain virus infections, and by a process demonstrated to inactivate and/or remove certain viruses during manufacturing [see Warnings and Precautions (5.2)]. Symptoms of a possible virus infection include headache, fever, nausea, vomiting, weakness, malaise, diarrhea, or, in the case of hepatitis, jaundice.
- Inform patients that administration of GLASSIA has been demonstrated to raise the plasma level of Alpha1-PI, but that the effect of this augmentation on the frequency of pulmonary exacerbations and on the rate of progression of emphysema has not been established by clinical trials.

Self-administration – If self-administration is deemed appropriate, ensure that the patient/caregiver receives detailed instructions and adequate training on how to administer in the home or other appropriate setting and has demonstrated the ability to independently administer GLASSIA.

- Ensure the patient/caregiver understands the importance of weekly infusions to raise the plasma level of Alpha1-PI.
- Ensure that the patient/caregiver has access to and has received training in the administration of subcutaneous epinephrine and/or other appropriate supportive therapy for the treatment of any acute anaphylactic or anaphylactoid reaction.
- Advise the patient/caregiver to report any adverse reactions or problems following GLASSIA administration to their physician or healthcare provider.
- Instruct the patient/caregiver to keep a treatment infusion log. This infusion log should include information such as, the lot number, the time, date, and any reactions.

Manufactured by:
Takeda Pharmaceuticals U.S.A., Inc.
Cambridge, MA 02142 USA
U.S. License No. 1898

GLASSIA® is a registered trademark of Kamada Ltd., used under license.

Takeda and are registered trademarks of Takeda Pharmaceutical Company Limited.

©2025 Takeda Pharmaceutical Company Limited. All rights reserved.

GLA378

Patient Information
GLASSIA®
(Alpha1-Proteinase Inhibitor (Human)) Injection,
For Intravenous Use

The following summarizes important information about GLASSIA (pronounced glass-see-ă). Please read it carefully before using this medicine. This information does not take the place of talking with your healthcare professional, and it does not include all of the important information about GLASSIA. If you have any questions after reading this, ask your healthcare professional.

What is GLASSIA?

GLASSIA is a liquid medicine containing human Alpha1-Proteinase Inhibitor (Alpha1-PI) also known as alpha1-antitrypsin (AAT), which is purified from human blood. The main purpose of infusing GLASSIA is to increase the levels of the AAT protein in your blood and lungs. AAT protein protects the lung tissue by blocking certain enzyme-caused damage. Such damage can lead to severe lung disease, such as emphysema.

Limitations of Use:

- The effects of increasing the AAT protein levels with GLASSIA or any other Alpha1-PI product on worsening pulmonary function and progression of emphysema have not been proven in clinical trials.
- The long-term effects of AAT replacement and maintenance therapy with GLASSIA have not been studied.
- GLASSIA is not intended as a therapy in individuals with lung disease other than severe Alpha1-PI deficiency.

Who should not take GLASSIA?

You should not use GLASSIA if you:

- Have IgA deficiency with antibodies to IgA
- Have had a severe allergic reaction to human Alpha1-PI products

What is the most important information that I should know about GLASSIA?

Severe allergic reactions can occur with GLASSIA. Your doctor will inform you about signs of allergic reactions which include hives, swelling in the mouth or throat, itching, tightness in the chest, trouble breathing, wheezing, faintness, low blood pressure, or serious allergic reaction. If you have any of these reactions, discontinue use of the product and contact your physician and/or seek immediate emergency care, depending on the severity of the reaction.

If you or your caregiver will be administering GLASSIA outside a healthcare setting, ask your doctor about an epinephrine pen and/or other supportive care for certain severe allergic reactions. Ask your doctor to make sure you receive training on how and when to use any prescribed supportive care medicine and keep it close at hand when administering GLASSIA.

How should I take GLASSIA?

- GLASSIA is given directly into the bloodstream.
- You can get GLASSIA at your healthcare professional's office, clinic, hospital, or delivered directly to your home by a healthcare professional from a limited network of specialty pharmacy providers.
- Your healthcare professional will decide if self-infusion in your home is right for you. You should be trained on how to do infusions by your healthcare professional.

What should I tell my healthcare professional before I start using GLASSIA?

Before starting GLASSIA, tell your healthcare professional if you:

- Have IgA deficiency with antibodies to IgA.
- Have a history of severe allergic reactions to Alpha1-PI products.

What are the possible or reasonably likely side effects of GLASSIA?

- A possible side effect to GLASSIA is worsening or flare-up of your chronic obstructive pulmonary disease (COPD) in which your breathing gets worse than usual.
- Call your healthcare professional or go to your emergency department right away if you get: Hives, swelling in the mouth or throat, itching, chest tightness, trouble breathing, wheezing, fainting or dizziness. These could be signs of a serious allergic reaction.
- The most common side effects are headache and upper respiratory tract infections. Other possible side effects of GLASSIA include: cough, sinus infection, chest discomfort, dizziness, increased liver enzymes, shortness of breath, nausea, and fatigue.

These are not all of the possible side effects for GLASSIA. You can ask your healthcare professional for information that is provided to healthcare professionals. Talk to your healthcare professional about any side effects that bother you or that don't go away.

How do I store GLASSIA?

Store GLASSIA refrigerated or at room temperature.

- You can store GLASSIA in the refrigerator (36°F to 46°F [2°C to 8°C]). Do not freeze.
- You can store GLASSIA at room temperature (up to 77°F [25°C]) for up to one month. You must use GLASSIA within one month once you remove it from the refrigerator. Do not re-refrigerate GLASSIA once the product has been stored at room temperature.
- Keep the GLASSIA vial in the box until you are ready to administer the product.

Check the expiration date on the carton and vial label. Do not use GLASSIA after the expiration date.

Manufactured by:
Takeda Pharmaceuticals U.S.A., Inc.
Cambridge, MA 02142 USA
U.S. License No. 1898

GLASSIA® is a registered trademark of Kamada Ltd., used under license.

Takeda and are registered trademarks of Takeda Pharmaceutical Company Limited.

©2025 Takeda Pharmaceutical Company Limited. All rights reserved.

Revised: February 2025

GLA378

Detailed Instructions For Administration
GLASSIA®
(Alpha1-Proteinase Inhibitor (Human)) Injection,
For Intravenous Use

Do not attempt to do an infusion to yourself unless you or your caregiver have been taught how by your healthcare professional.

Always follow the specific instructions given by your healthcare professional. The steps listed below are general guidelines for using GLASSIA. If you are unsure of the procedures, call your healthcare professional before using.

Prepare a clean flat surface and gather all the materials you will need for the infusion. Check the expiration date, and let the vial of GLASSIA warm up to room temperature. Do not apply heat, place in hot water, or microwave. Wash your hands and put on clean exam gloves. If you are infusing yourself at home, the use of gloves is optional.

1. Check the vial(s) of GLASSIA:
  - Do not use if the protective cap is missing or broken.
  - Look at the color: it should be clear and colorless to yellow-green.
  - Do not use if the solution is cloudy.
  - It may contain a few (protein) particles.
  - Do not shake the vial(s).
2. Gather all supplies
  - Gather all supplies: vial(s) of GLASSIA as prescribed and infusion supplies (not provided): tourniquet, alcohol swabs, intravenous needle set (butterfly), vented spike(s), 5 micron in-line filter (minimum of 32 mm diameter is recommended for optimal performance), 60 mL sterile syringe(s), transfer needle(s), sterile intravenous infusion container (bag) (if necessary), administration infusion set, extension set (if necessary), bandage, tape, sterile gauze, sharps container, IV pole or hook, clean gloves (if necessary) and infusion log.
  - If a drip chamber is used it must not contain a filter.
  - If your doctor has prescribed epinephrine pen and/or other supportive care for certain severe allergic symptoms, keep it close at hand during your infusion. Carefully follow your doctor's instructions and training if you have to administer the prescribed medicine for a severe allergic reaction.
  - Wash your hands and allow them to dry.
  - Apply gloves as directed by your healthcare professional.
    Open supplies as shown by your healthcare professional.
3. Prepare the vials(s) for infusion as directed by your healthcare professional:
  - Remove the protective cap from the vial.
  - Wipe the stoppers of each vial that you will need for your dose with a sterile alcohol swab and allow the stopper to dry.
  - As directed by your healthcare professional, you may infuse directly from the vial. Peel clear plastic hanger from vial label and hang the vial from an IV pole or hook or pool the recommended number of vials of GLASSIA into an empty, sterile container (bag) for intravenous infusion. Use the product within 3 hours of entering the vial(s) or pooling into a sterile container (bag).
  If you are pooling into a sterile container (bag):
  - Attach a vented spike to a sterile syringe.
  Insert the vented spike into the center of the GLASSIA vial.
  - Turn the vial upside down and pull back on the plunger to pull the GLASSIA solution into the syringe(s).
  - Twist to remove the syringe from the vented spike.
  - Point the syringe tip up and gently push the plunger of the syringe to remove the air.
  - Attach a transfer needle to the filled syringe.
  - Wipe the injection port on the empty sterile container (bag) with an alcohol swab before each needle insertion. Use a new alcohol swab for each vial.
  - Remove protective cover of needle and insert the needle into the injection port and fill the empty bag. Avoid touching the exposed needle.
  - Remove the needle from the injection port and discard the syringe and needle in a sharps container.
  - Repeat these steps, if using multiple vials to achieve the desired dose as directed by your healthcare professional, using a new vented spike and transfer needle with each vial.
4. Prepare the infusion set:
  - Close the roller clamp on the IV infusion set.
  - Attach an in-line 5 micron filter to the end of the IV infusion set.
  - Attach an extension set (if necessary) to in-line filter.
  - Remove cap from the IV infusion set spike and remove the cover from the infusion port on the bag containing GLASSIA. Avoid touching the exposed spike or infusion port.
  - Insert the spike more than halfway into the infusion port on the containing GLASSIA by twisting and pushing.
  - Hang the pooling bag from an IV pole or hook.
  - Squeeze the drip chamber until it is half-full and fill the IV tubing with GLASSIA solution by releasing the roller clamp. Close clamp when the solution reaches the end of the extension set.
5. Prepare the infusion site(s):
  - Connect the saline syringe to the needle set (butterfly) and fill.
  - Select an infusion site as directed by your healthcare professional.
  - Rotate infusion sites as directed.
  - Apply a tourniquet.
  - Get the injection site ready by wiping the skin well with an alcohol swab (or other suitable solution suggested by your healthcare provider) and wait for the skin to dry. Do not touch or blow on the cleaned infusion site.
6. Insert and secure the intravenous needle set as directed by your healthcare professional.
  - Release the tourniquet.
  - Draw back slightly on syringe to check for blood return. The presence of blood means the needle placement is correct. If there is no blood present, repeat steps.
  - Flush the intravenous needle set (butterfly) with normal saline.
  - Remove the saline flush syringe and attach the IV infusion set filled with GLASSIA solution.
7. Follow your healthcare professional's instructions for infusing GLASSIA:
  - Open the roller clamp and administer GLASSIA solution at room temperature at a rate as directed by your healthcare professional. The maximum recommended infusion rate for GLASSIA is 0.2 milliliter per kilogram body weight per minute which will take approximately 15 minutes to infuse.
  - Check infusion site occasionally throughout the infusion to make sure that the drug is flowing and there is no bleeding.
  - When the infusion is complete, take the needle out of the vein and discard in a sharps container. Use sterile gauze to put pressure on the infusion site for several minutes and then apply a sterile bandage.
  - Do not recap the intravenous needle set. Place the needle set in a sharps container for proper disposal. Do not dispose of these supplies in ordinary household trash.
8. Record the infusion:
  - Write down the product lot number and expiration date in your treatment record/infusion log.
  - Write down the date, time (start and end), dose, site(s) of infusion (to assist in rotating sites) and any reactions after each infusion. Report all reactions to your healthcare professional.
  - Throw away all open vials, and any unused solution into a sharps container, as recommended by your healthcare professional.

Manufactured by:
Takeda Pharmaceuticals U.S.A., Inc.
Cambridge, MA 02142 USA
U.S. License No. 1898

GLASSIA® is a registered trademark of Kamada Ltd., used under license.

Takeda and are registered trademarks of Takeda Pharmaceutical Company Limited.

©2025 Takeda Pharmaceutical Company Limited. All rights reserved.

Revised: February 2025

GLA378

PRINCIPAL DISPLAY PANEL - 50 ml Vial Label

NDC 0944-2884-02

ALPHA-1 PROTEINASE
INHIBITOR (HUMAN)
GLASSIA®

For Intravenous Administration Only

Injection Solution

50 mL

Takeda

PRINCIPAL DISPLAY PANEL - 50 ml Vial Carton

NDC 0944-2884-01

ALPHA-1 PROTEINASE
INHIBITOR [HUMAN]
GLASSIA®

Injection Solution

For Intravenous Administration Only

50 mL

Takeda

PRINCIPAL DISPLAY PANEL - 200 ml Vial Label

NDC 0944-2884-04

ALPHA-1 PROTEINASE
INHIBITOR (HUMAN)
GLASSIA®

For Intravenous Administration
Only

200 mL

Injection Solution

Takeda

PRINCIPAL DISPLAY PANEL - 200 ml Vial Carton

NDC 0944-2884-03

ALPHA-1 PROTEINASE
INHIBITOR [HUMAN]
GLASSIA®

Injection Solution

For Intravenous Administration Only

200 mL

Takeda

PRINCIPAL DISPLAY PANEL - 250 ml Vial Label

NDC 0944-2884-06

ALPHA-1 PROTEINASE
INHIBITOR (HUMAN)
GLASSIA®

For Intravenous Administration
Only

250 mL

Injection Solution

Takeda

PRINCIPAL DISPLAY PANEL - 250 ml Vial Carton

NDC 0944-2884-05

ALPHA-1 PROTEINASE
INHIBITOR [HUMAN]
GLASSIA®

Injection Solution

For Intravenous Administration Only

250 mL

Takeda